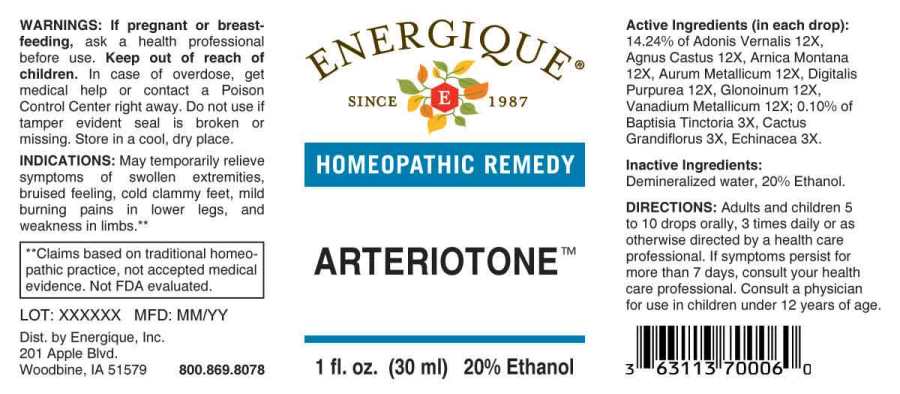 DRUG LABEL: Arteriotone
NDC: 44911-0230 | Form: LIQUID
Manufacturer: Energique, Inc.
Category: homeopathic | Type: HUMAN OTC DRUG LABEL
Date: 20240716

ACTIVE INGREDIENTS: BAPTISIA TINCTORIA ROOT 3 [hp_X]/1 mL; SELENICEREUS GRANDIFLORUS STEM 3 [hp_X]/1 mL; ECHINACEA ANGUSTIFOLIA WHOLE 3 [hp_X]/1 mL; ADONIS VERNALIS WHOLE 12 [hp_X]/1 mL; CHASTE TREE FRUIT 12 [hp_X]/1 mL; ARNICA MONTANA WHOLE 12 [hp_X]/1 mL; GOLD 12 [hp_X]/1 mL; DIGITALIS 12 [hp_X]/1 mL; NITROGLYCERIN 12 [hp_X]/1 mL; VANADIUM 12 [hp_X]/1 mL
INACTIVE INGREDIENTS: WATER; ALCOHOL

DRUG FACTS:

ACTIVE INGREDIENTS:

(in each drop): 14.24% of Adonis Vernalis 12X, Agnus Castus 12X, Arnica Montana 12X, Aurum Metallicum 12X, Digitalis Purpurea 12X, Glonoinum 12X, Vanadium Metallicum 12X; 0.10% of Baptisia Tinctoria 3X, Cactus Grandiflorus 3X, Echinacea (Angustifolia) 3X.

INDICATIONS:

May temporarily relieve symptoms of swollen extremities, bruised feeling, cold clammy feet, mild burning pains in leg, and weakness in limbs.**

**Claims based on traditional homeopathic practice, not accepted medical evidence. Not FDA evaluated.

WARNINGS:

If pregnant or breast-feeding, ask a health professional before use.

Keep out of reach of children. In case of overdose, get medical help or contact a Poison Control Center right away.

Do not use if tamper evident seal is broken or missing. Store in a cool, dry place.

KEEP OUT OF REACH OF CHILDREN:

In case of overdose, get medical help or contact a Poison Control Center right away.

DIRECTIONS:

Adults and children 5 to 10 drops orally, 3 times daily or as otherwise directed by a health care professional. If symptoms persist for more than 7 days, consult your health care professional. Consult a physician for use in children under 12 years of age.

INDICATIONS:

May temporarily relieve symptoms of swollen extremities, bruised feeling, cold clammy feet, mild burning pains in leg, and weakness in limbs.**

**Claims based on traditional homeopathic practice, not accepted medical evidence. Not FDA evaluated.

INACTIVE INGREDIENTS:

Demineralized water, 20% Ethanol.

QUESTIONS:

Dist. by Energique, Inc.

201 Apple Blvd

Woodbine, IA 51579 800-869-8078

PACKAGE LABEL DISPLAY:

ENERGIQUE
SINCE 1987
HOMEOPATHIC REMEDY
ARTERIOTONE
1 fl. oz. (30 ml)